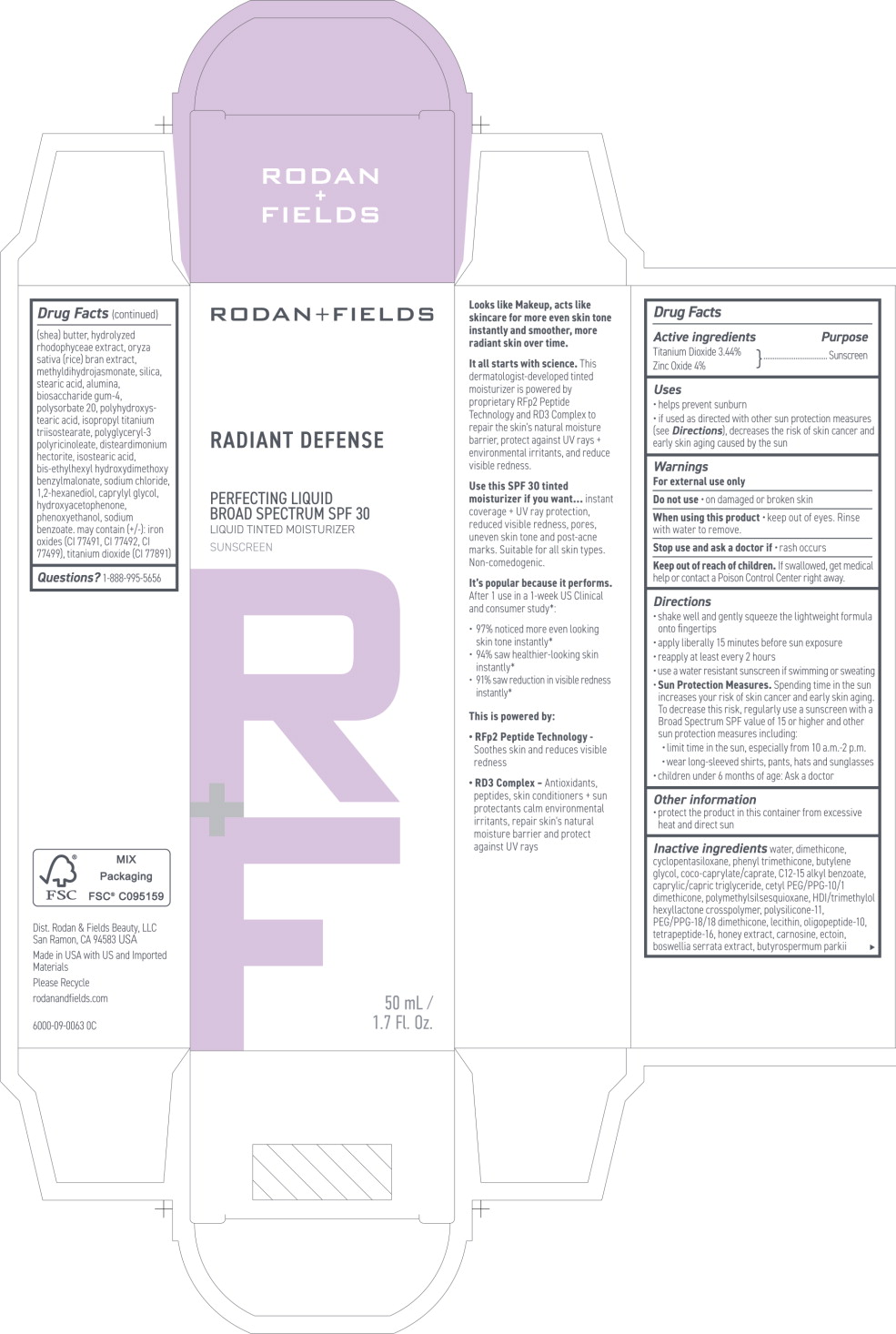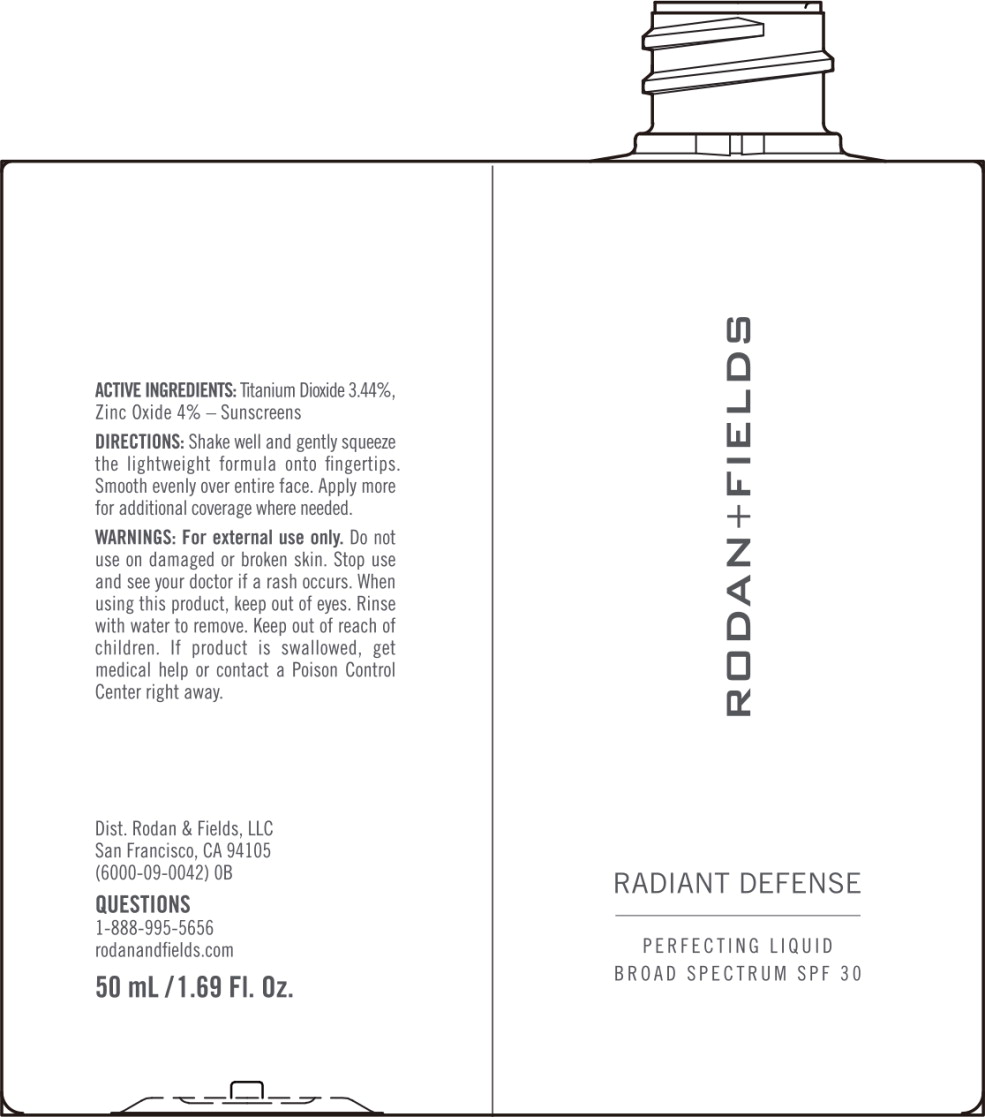 DRUG LABEL: Radiant Defense Perfecting Liquid Broad Spectrum SPF 30 - Shell
NDC: 14222-2030 | Form: LOTION
Manufacturer: Rodan & Fields
Category: otc | Type: HUMAN OTC DRUG LABEL
Date: 20251219

ACTIVE INGREDIENTS: Titanium Dioxide 3.44 g/100 mL; Zinc Oxide 4.0 g/100 mL
INACTIVE INGREDIENTS: 1,2-HEXANEDIOL; ALUMINUM OXIDE; BIOSACCHARIDE GUM-4; BIS-ETHYLHEXYL HYDROXYDIMETHOXY BENZYLMALONATE; INDIAN FRANKINCENSE; BUTYLENE GLYCOL; SHEA BUTTER; ALKYL (C12-15) BENZOATE; MEDIUM-CHAIN TRIGLYCERIDES; CAPRYLYL GLYCOL; CARNOSINE; CETYL PEG/PPG-10/1 DIMETHICONE (HLB 3); COCO-CAPRYLATE/CAPRATE; CYCLOMETHICONE 5; DIMETHICONE; DISTEARDIMONIUM HECTORITE; ECTOINE; HEXAMETHYLENE DIISOCYANATE/TRIMETHYLOL HEXYLLACTONE CROSSPOLYMER; HONEY; HYDROXYACETOPHENONE; ISOPROPYL TITANIUM TRIISOSTEARATE; ISOSTEARIC ACID; LECITHIN, SOYBEAN; METHYL DIHYDROJASMONATE (SYNTHETIC); OLIGOPEPTIDE-10; RICE BRAN; PEG/PPG-18/18 DIMETHICONE; PHENOXYETHANOL; PHENYL TRIMETHICONE; POLYHYDROXYSTEARIC ACID (2300 MW); POLYMETHYLSILSESQUIOXANE (4.5 MICRONS); POLYSORBATE 20; SILICON DIOXIDE; SODIUM BENZOATE; SODIUM CHLORIDE; STEARIC ACID; WATER

Drug Facts

Active ingredients

Titanium Dioxide 3.44%

Zinc Oxide 4%

Purpose

Sunscreen

Sunscreen

Uses

- helps prevent sunburn
- if used as directed with other sun protection measures (see Directions]. decreases the risk of skin cancer and early skin aging caused by the sun

Warnings

For external use only

Do not use

- on damaged or broken skin

When using this product

- keep out of eyes. Rinse with water to remove.

Stop use and ask a doctor if

- rash occurs

Keep out of reach of children. If swallowed, get medical help or contact a Poison Control Center right away.

Directions

- shake well and gently squeeze the lightweight formula onto fingertips
- apply liberally 15 minutes before sun exposure
- reapply at least every 2 hours
- use a water resistant sunscreen if swimming or sweating
- Sun Protection Measures. Spending time in the sun increases your risk of skin cancer and early skin aging. To decrease this risk, regularly use a sunscreen with a Broad Spectrum SPF value of 15 or higher and other sun protection measures including:
  - limit time in the sun, especially from 10 a.m.-2 p.m.
  - wear long-sleeved shirts, pants, hats and sunglasses
  - children under 6 months of age: Ask a doctor

Other information

- protect the product in this container from excessive heat and direct sun

Inactive ingredients

water, dimethicone, cyclopentasiloxane, phenyl trimethicone, butylene glycol, coco-caprylate/caprate, C12-15 alkyl benzoate, caprylic/capric triglyceride, cetyl PEG/PPG-10/1 dimethicone, polymethylsilsesquioxane, HDI/trimethylol hexyllactone crosspolymer, polysilicone-11, PEG/PPG-18/18 dimethicone, lecithin, oligopeptide-10, tetrapeptide-16, honey extract, carnosine, ectoin, boswellia serrata extract, butyrospermum parkii (shea) butter, hydrolyzed rhodophyceae extract, oryza sativa (rice) bran extract, methyldihydrojasmonate, silica, stearic acid, alumina, biosaccharide gum-4, polysorbate 20, polyhydroxystearic acid, isopropyl titanium triisostearate, polyglyceryl-3 polyricinoleate, disteardimonium hectorite, isostearic acid, bis-ethylhexyl hydroxydimethoxy benzylmalonate, sodium chloride, 1,2-hexanediol, caprylyl glycol, hydroxyacetophenone, phenoxyethanol, sodium benzoate, may contain (+/-): iron oxides (CI 77491, CI 77492, CI 77499), titanium dioxide (CI 77891)

Questions?

1-888-995-5656

Principal Display Panel – 50 mL Cream Box Label

RODAN+FIELDS

RADIANT DEFENSE

PERFECTING LIQUID
BROAD SPECTRUM SPF 30

LIQUID TINTED MOISTURZER
SUNSCREEN

50mL/1.70 Fl. Oz.

Cream/1.5

Principal Display Panel – 50 mL Cream Bottle Label

RODAN+FIELDS

RADIANT DEFENSE

PERFECTING LIQUID
BROAD SPECTRUM SPF 30

Cream/1.5

Principal Display Panel – 50 mL Shell Box Label

RODAN+FIELDS

RADIANT DEFENSE

PERFECTING LIQUID
BROAD SPECTRUM SPF 30

LIQUID TINTED MOISTURZER
SUNSCREEN

50mL/1.70 Fl. Oz.

Shell/1

Principal Display Panel – 50 mL Shell Bottle Label

RODAN+FIELDS

RADIANT DEFENSE

PERFECTING LIQUID
BROAD SPECTRUM SPF 30

Shell/1

Principal Display Panel – 50 mL Beige Box Label

RODAN+FIELDS

RADIANT DEFENSE

PERFECTING LIQUID
BROAD SPECTRUM SPF 30

LIQUID TINTED MOISTURZER
SUNSCREEN

50mL/1.70 Fl. Oz.

Beige/2

Principal Display Panel – 50 mL Beige Bottle Label

RODAN+FIELDS

RADIANT DEFENSE

PERFECTING LIQUID
BROAD SPECTRUM SPF 30

Beige/2

Principal Display Panel – 50 mL Sand Box Label

RODAN+FIELDS

RADIANT DEFENSE

PERFECTING LIQUID
BROAD SPECTRUM SPF 30

LIQUID TINTED MOISTURZER
SUNSCREEN

50mL/1.70 Fl. Oz.

Sand/3

Principal Display Panel – 50 mL Sand Bottle Label

RODAN+FIELDS

RADIANT DEFENSE

PERFECTING LIQUID
BROAD SPECTRUM SPF 30

Sand/3

Principal Display Panel – 50 mL Honey Box Label

RODAN+FIELDS

RADIANT DEFENSE

PERFECTING LIQUID
BROAD SPECTRUM SPF 30

LIQUID TINTED MOISTURZER
SUNSCREEN

50mL/1.70 Fl. Oz.

Honey/4.5

Principal Display Panel – 50 mL Honey Bottle Label

RODAN+FIELDS

RADIANT DEFENSE

PERFECTING LIQUID
BROAD SPECTRUM SPF 30

Honey/4.5

Principal Display Panel – 50 mL Golden Box Label

RODAN+FIELDS

RADIANT DEFENSE

PERFECTING LIQUID
BROAD SPECTRUM SPF 30

LIQUID TINTED MOISTURZER
SUNSCREEN

50mL/1.70 Fl. Oz.

Golden/4

Principal Display Panel – 50 mL Golden Bottle Label

RODAN+FIELDS

RADIANT DEFENSE

PERFECTING LIQUID
BROAD SPECTRUM SPF 30

Golden/4

Principal Display Panel – 50 mL Almond Box Label

RODAN+FIELDS

RADIANT DEFENSE

PERFECTING LIQUID
BROAD SPECTRUM SPF 30

LIQUID TINTED MOISTURZER
SUNSCREEN

50mL/1.70 Fl. Oz.

Almond/5

Principal Display Panel – 50 mL Almond Bottle Label

RODAN+FIELDS

RADIANT DEFENSE

PERFECTING LIQUID
BROAD SPECTRUM SPF 30

Almond/5

Principal Display Panel – 50 mL Caramel Box Label

RODAN+FIELDS

RADIANT DEFENSE

PERFECTING LIQUID
BROAD SPECTRUM SPF 30

LIQUID TINTED MOISTURZER
SUNSCREEN

50mL/1.70 Fl. Oz.

Caramel/5.5

Principal Display Panel – 50 mL Caramel Bottle Label

RODAN+FIELDS

RADIANT DEFENSE

PERFECTING LIQUID
BROAD SPECTRUM SPF 30

Caramel/5.5

Principal Display Panel – 50 mL Espresso Box Label

RODAN+FIELDS

RADIANT DEFENSE

PERFECTING LIQUID
BROAD SPECTRUM SPF 30

LIQUID TINTED MOISTURZER
SUNSCREEN

50mL/1.70 Fl. Oz.

Espresso/6

Principal Display Panel – 50 mL Espresso Bottle Label

RODAN+FIELDS

RADIANT DEFENSE

PERFECTING LIQUID
BROAD SPECTRUM SPF 30

Espresso/6

Principal Display Panel – 50 mL Truffle Box Label

RODAN+FIELDS

RADIANT DEFENSE

PERFECTING LIQUID
BROAD SPECTRUM SPF 30

LIQUID TINTED MOISTURZER
SUNSCREEN

50mL/1.70 Fl. Oz.

Truffle/7

Principal Display Panel – 50 mL Truffle Bottle Label

RODAN+FIELDS

RADIANT DEFENSE

PERFECTING LIQUID
BROAD SPECTRUM SPF 30

Truffle/7